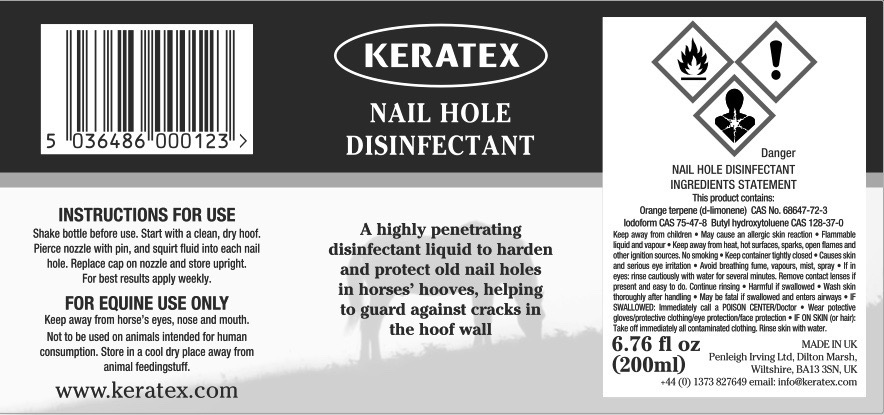 DRUG LABEL: Keratex
NDC: 27426-030 | Form: LIQUID
Manufacturer: Penleigh Irving Ltd
Category: animal | Type: OTC ANIMAL DRUG LABEL
Date: 20181217

ACTIVE INGREDIENTS: LIMONENE, (+)- 0.84 g/1 mL; IODOFORM 4.1 g/1 mL

SAFE HANDLING WARNING

Keep away from children. May cause an allergic skin reaction. Flammable liquid and vapour. Keep away from heat, hot surfaces, sparks, open flames and other ignition sources. No smoking. Keep container tightly closed. Causes skin and serious eye irritation. Avoid breathing fume, vapours, mist, spray. If in eyes: rinse cautiously with water for several minutes. Remove contact lenses if present and easy to do. Continue rinsing. Harmful if swallowed. Wash skin thoroughly after handling. May be fatal if swallowed and enters airways. IF SWALLOWED: Immediately call a POISON CENTER/Doctor. Wear protective gloves/protective clothing/Eye protection/face protection. IF ON SKIN (or hair): Take off immediately all contaminated clothing. Rinse skin with water.

PACKAGE LABEL

Keratex Nail Hole Disinfectant

A highly penetrating disinfectant liquid to harden and protect old nail holes in horses' hooves, helping to guard against cracks in the hoof wall

Instructions for use: Shake bottle before use. Start with a clean dry hoof. Pierce nozzle with pin, and squirt fluid into each nail hole. Replace cap on nozzle and store upright. For best results apply weekly.

Nail Hole Disinfectant Ingredients Statement. This product contains: Orange terpene (d-limonene) CAS No. 68647-72-3. Iodoform CAS No. 75-47-8. Butyl hydroxytoluene CAS NO. 128-37-0.

For Equine Use Only. Keep away from the horse’s eyes, nose and mouth. Not to be used on animals intended for human consumption. Store in a cool dry place away from animal feedingstuff.

6.76 fl oz (200ml)

MADE IN UK

Penleigh Irving Ltd.

Dilton Marsh, Wiltshire, BK13 3SN, UK

+44 (0) 1373 827649 email: info@keratex.com

www.keratex.com